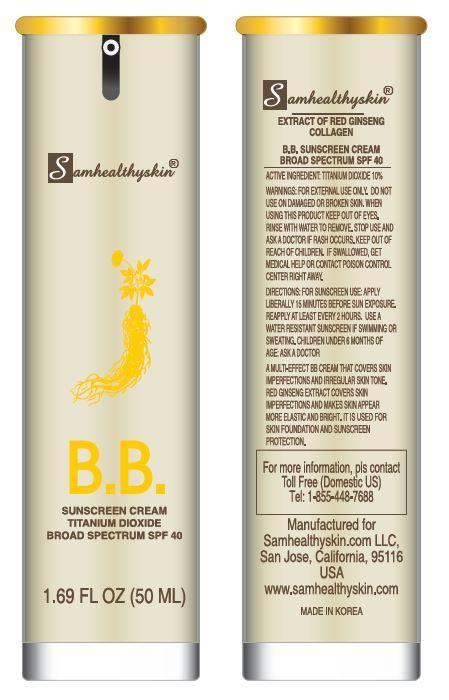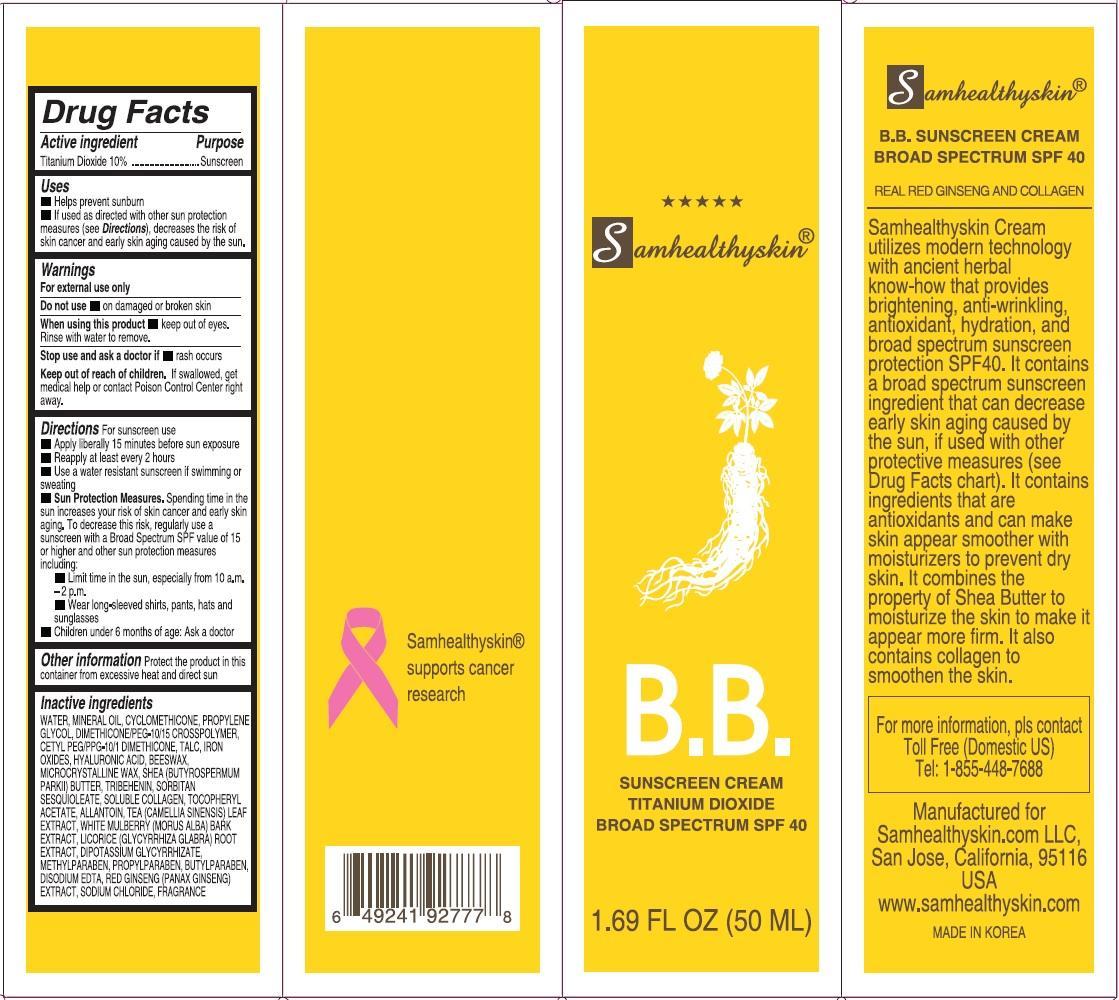 DRUG LABEL: Samhealthyskin B.B. SUNSCREEN BROAD SPECTRUM SPF 40
                
                
NDC: 57650-159 | Form: CREAM
Manufacturer: Samhealthyskin.COM LLC
Category: otc | Type: HUMAN OTC DRUG LABEL
Date: 20150811

ACTIVE INGREDIENTS: TITANIUM DIOXIDE 100 mg/1 mL
INACTIVE INGREDIENTS: WATER; MINERAL OIL; CYCLOMETHICONE; PROPYLENE GLYCOL; POLYETHYLENE GLYCOL 500; CETYL PEG/PPG-10/1 DIMETHICONE (HLB 2); TALC; FERRIC OXIDE RED; HYALURONIC ACID; YELLOW WAX; MICROCRYSTALLINE WAX; SHEA BUTTER; TRIBEHENIN; SORBITAN SESQUIOLEATE; MARINE COLLAGEN, SOLUBLE; .ALPHA.-TOCOPHEROL ACETATE; ALLANTOIN; GREEN TEA LEAF; MORUS ALBA BARK; LICORICE; GLYCYRRHIZINATE DIPOTASSIUM ; METHYLPARABEN; PROPYLPARABEN; BUTYLPARABEN; EDETATE DISODIUM; ASIAN GINSENG; SODIUM CHLORIDE

Samhealthyskin B.B. SUNSCREEN CREAM BROAD SPECTRUM SPF 40

Active ingredient

Titanium Dioxide 10%

Purpose

Sunscreen

Uses

- Helps prevent sunburn
- If used as directed with other sun protection measures (see Directions), decreases the risk of skin cancer and early skin aging caused by the sun.

Warnings

For external use only
Do not use on damaged or broken skin
When using this product

- keep out of eyes. Rinse with water to remove.

Stop use and ask a doctor if

- rash occurs

Keep out of reach of children.

If swallowed, get medical help or contact Poison Control Center right away.

Directions

For sunscreen use

- Apply liberally 15 minutes before sun exposure
- Reapply at least every 2 hours
- Use a water resistant sunscreen if swimming or sweating

Sun Protection Measures. Spending time in the sun increases your risk of skin cancer and early skin aging. To decrease this risk, regularly use a sunscreen with a Broad Spectrum SPF value of 15 or higher and other sun protection measures including:

- Limit time in the sun, especially from 10 a.m.– 2 p.m.
- Wear long-sleeved shirts, pants, hats and sunglasses

Children under 6 months of age: Ask a doctor

Other Information

Protect the product in this container from excessive heat and direct sun.

Inactive ingredients

WATER, MINERAL OIL, CYCLOMETHICONE, PROPYLENE GLYCOL, DIMETHICONE/PEG-10/15 CROSSPOLYMER, CETYL PEG/PPG-10/1 DIMETHICONE, TALC, IRON OXIDES, HYALURONIC ACID, BEESWAX, MICROCRYSTALLINE WAX, SHEA (BUTYROSPERMUM PARKII) BUTTER, TRIBEHENIN, SORBITAN SESQUIOLEATE, SOLUBLE COLLAGEN, TOCOPHERYL ACETATE, ALLANTOIN, TEA (CAMELLIA SINENSIS) LEAF EXTRACT, WHITE MULBERRY (MORUS ALBA) BARK EXTRACT, LICORICE (GLYCYRRHIZA GLABRA) ROOT EXTRACT, DIPOTASSIUM GLYCYRRHIZATE, ETHYLPARABEN, PROPYLPARABEN, BUTYLPARABEN, DISODIUM EDTA, RED GINSENG (PANAX GINSENG)EXTRACT, SODIUM CHLORIDE, FRAGRANCE